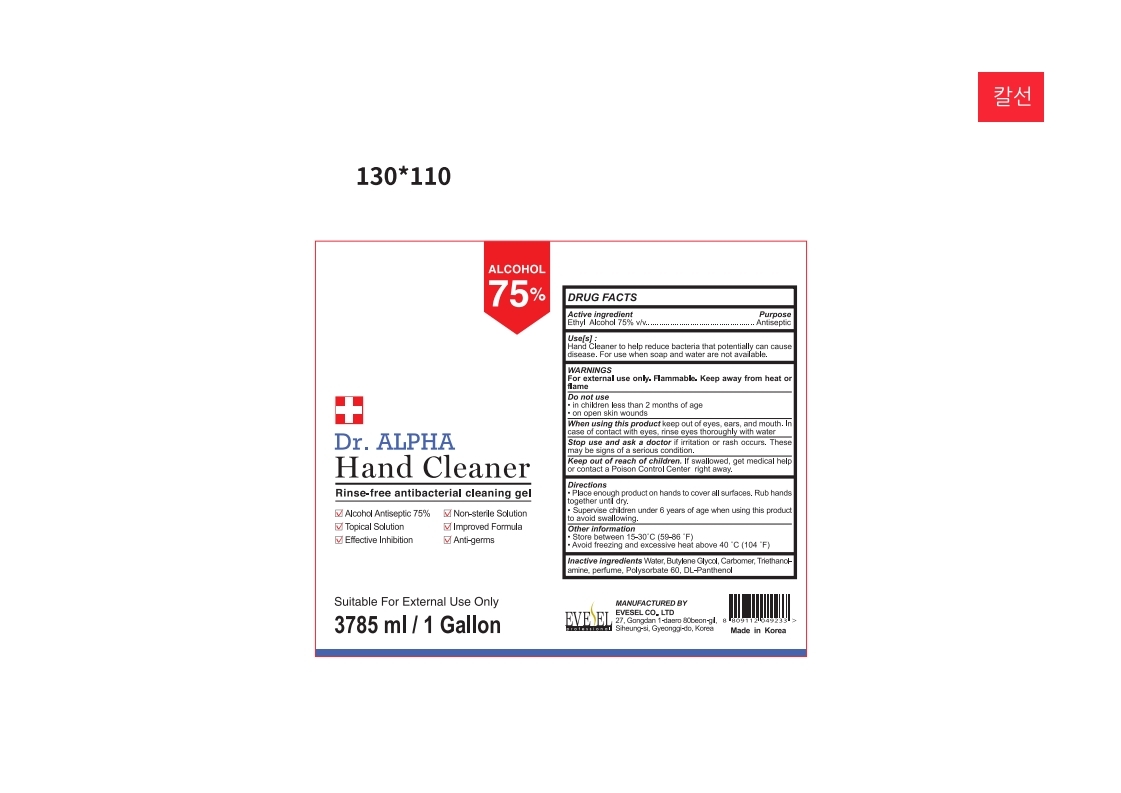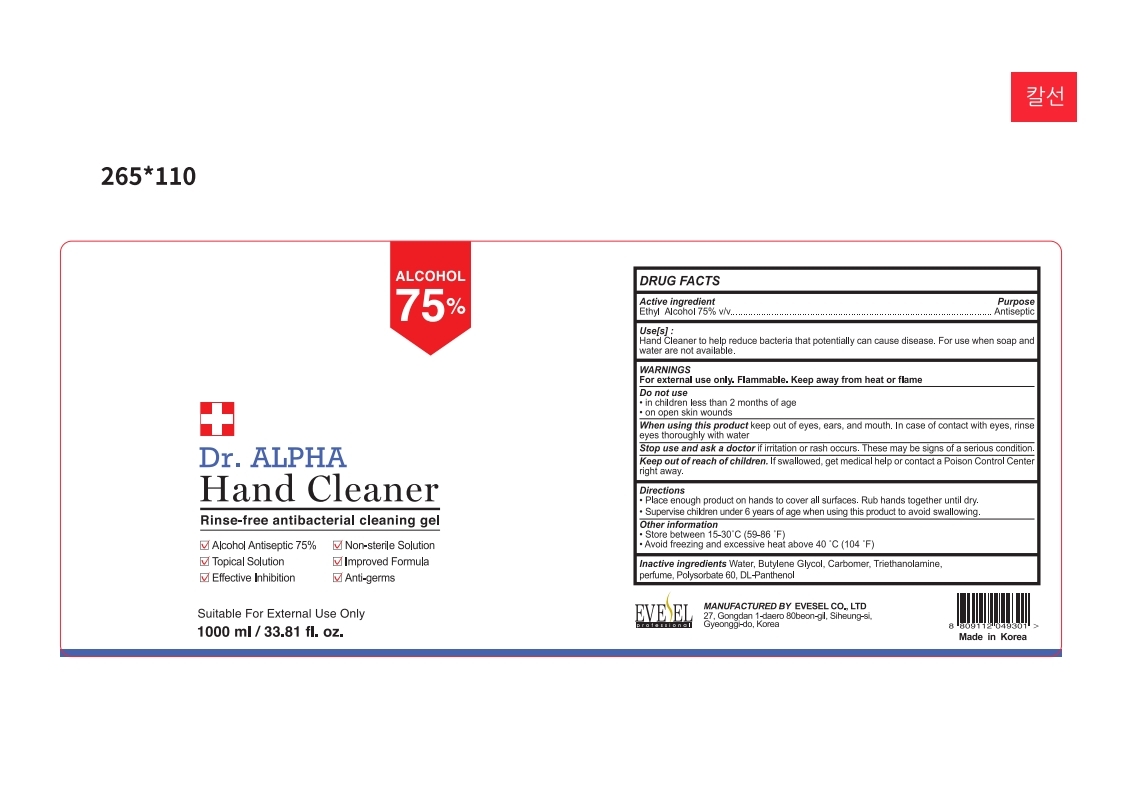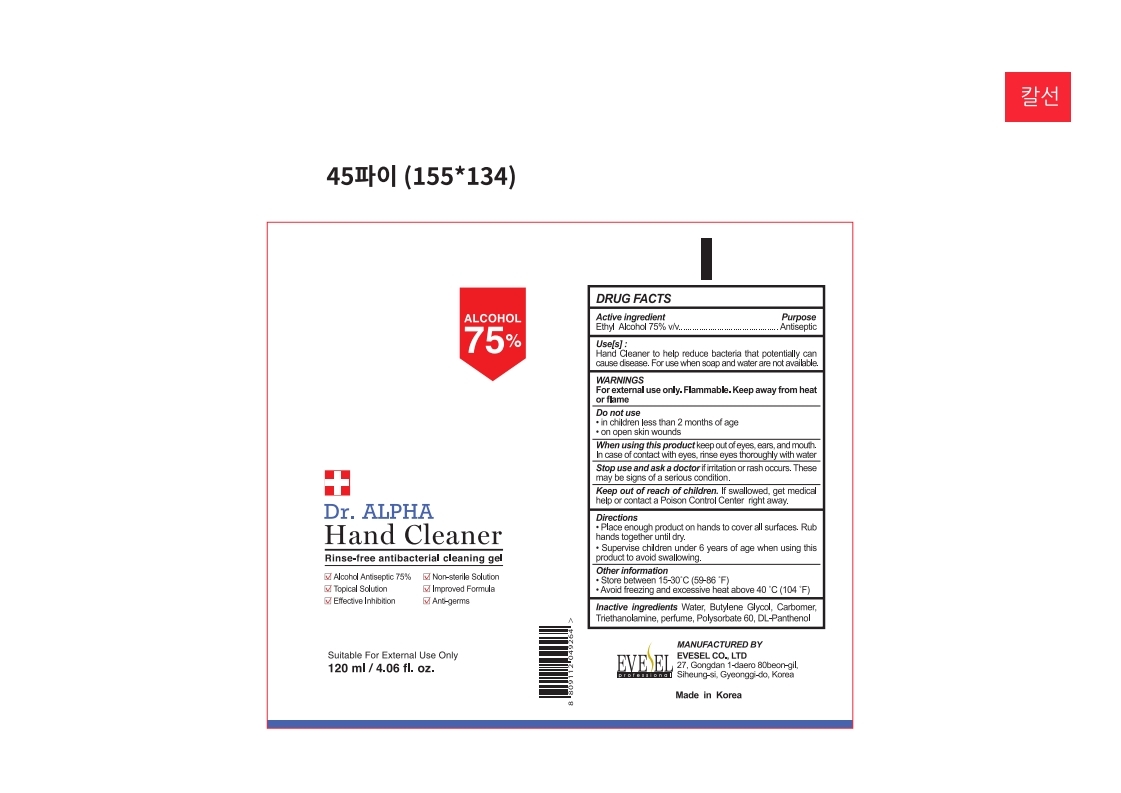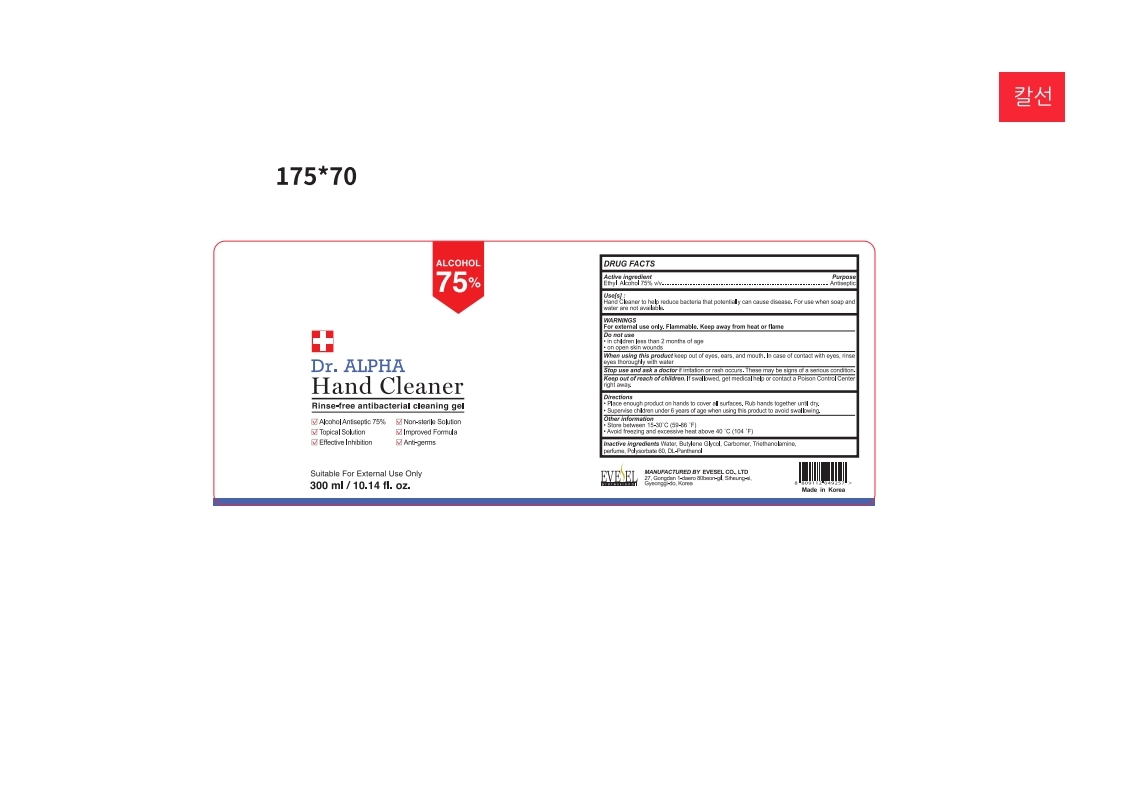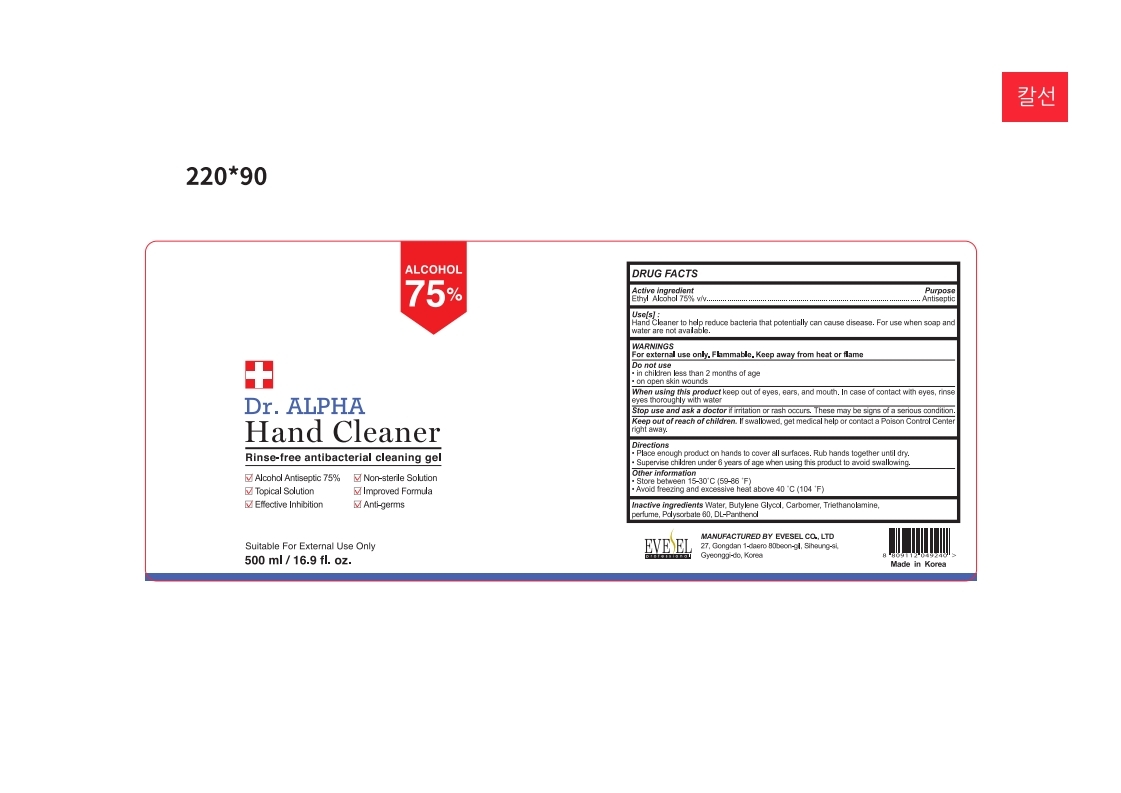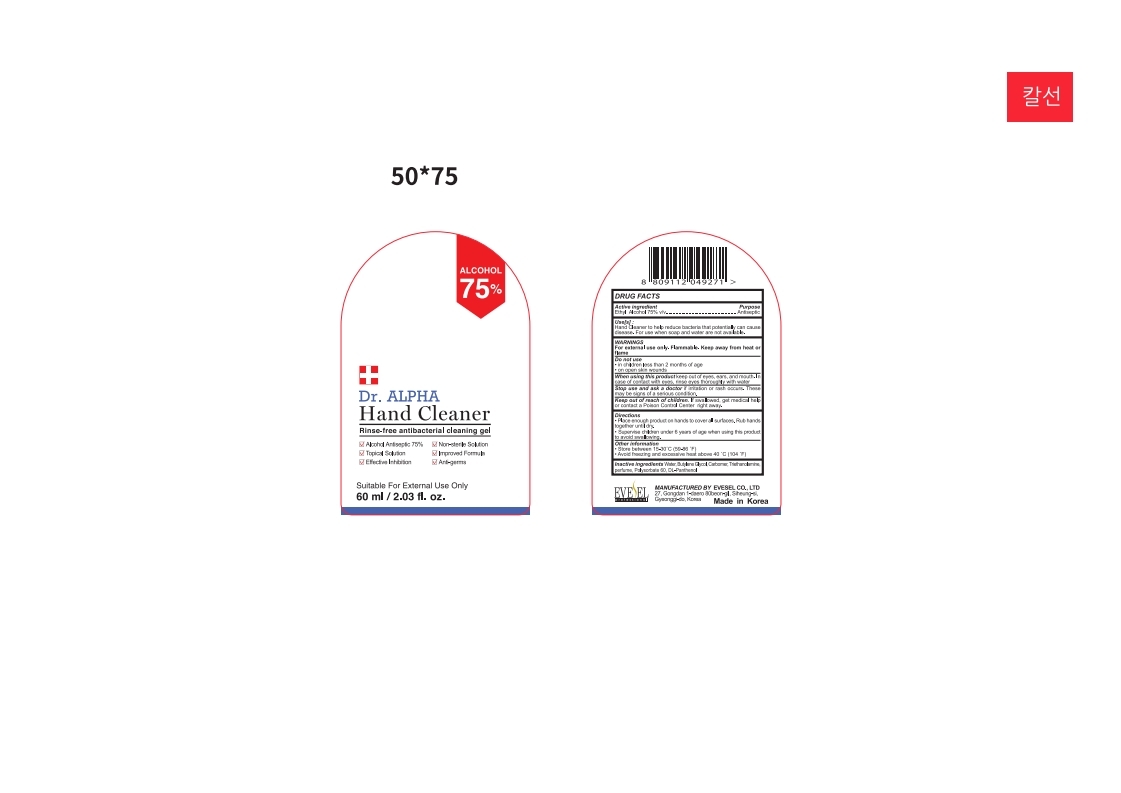 DRUG LABEL: Dr. Alpha Hand Cleaner
NDC: 78146-756 | Form: GEL
Manufacturer: EVESEL CO., LTD
Category: otc | Type: HUMAN OTC DRUG LABEL
Date: 20210109

ACTIVE INGREDIENTS: ALCOHOL 75 mL/100 mL
INACTIVE INGREDIENTS: TROLAMINE 0.2 mL/100 mL; BUTANEDIOL (MIXED ISOMERS) 1 mL/100 mL; CARBOMER 980 0.45 mL/100 mL; PANTHENOL 0.01 mL/100 mL; POLYSORBATE 60 0.05 mL/100 mL; WATER 23.2 mL/100 mL; CARBOMER HOMOPOLYMER TYPE A (ALLYL PENTAERYTHRITOL CROSSLINKED) 0.03 mL/100 mL

Dr. Alpha hand cleaner 75% Evesel

Active Ingredient(s)

Ethyl Alcohol 75% v/v. Purpose: Antiseptic

Purpose

Antiseptic, Hand Sanitizer

Use

Hand Sanitizer to help reduce bacteria that potentially can cause disease. For use when soap and water are not available.

Warnings

For external use only. Flammable. Keep away from heat or flame

Do not use

- in children less than 2 months of age
- on open skin wounds

When using this product keep out of eyes, ears, and mouth. In case of contact with eyes, rinse eyes thoroughly with water.
Stop use and ask a doctor if irritation or rash occurs. These may be signs of a serious condition.
Keep out of reach of children. If swallowed, get medical help or contact a Poison Control Center right away.

Stop use and ask a doctor if irritation or rash occurs. These may be signs of a serious condition.

Keep out of reach of children. If swallowed, get medical help or contact a Poison Control Center right away.

Directions

- Place enough product on hands to cover all surfaces. Rub hands together until dry.
- Supervise children under 6 years of age when using this product to avoid swallowing.

Other information

- Store between 15-30C (59-86F)
- Avoid freezing and excessive heat above 40C (104F)

Inactive ingredients

Alcohol, Water, Butylene Glycol, Carbomer, Triethanolamine, perfume, Polysorbate 60, DL-Panthenol